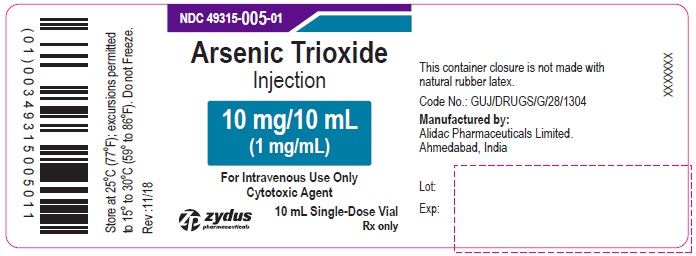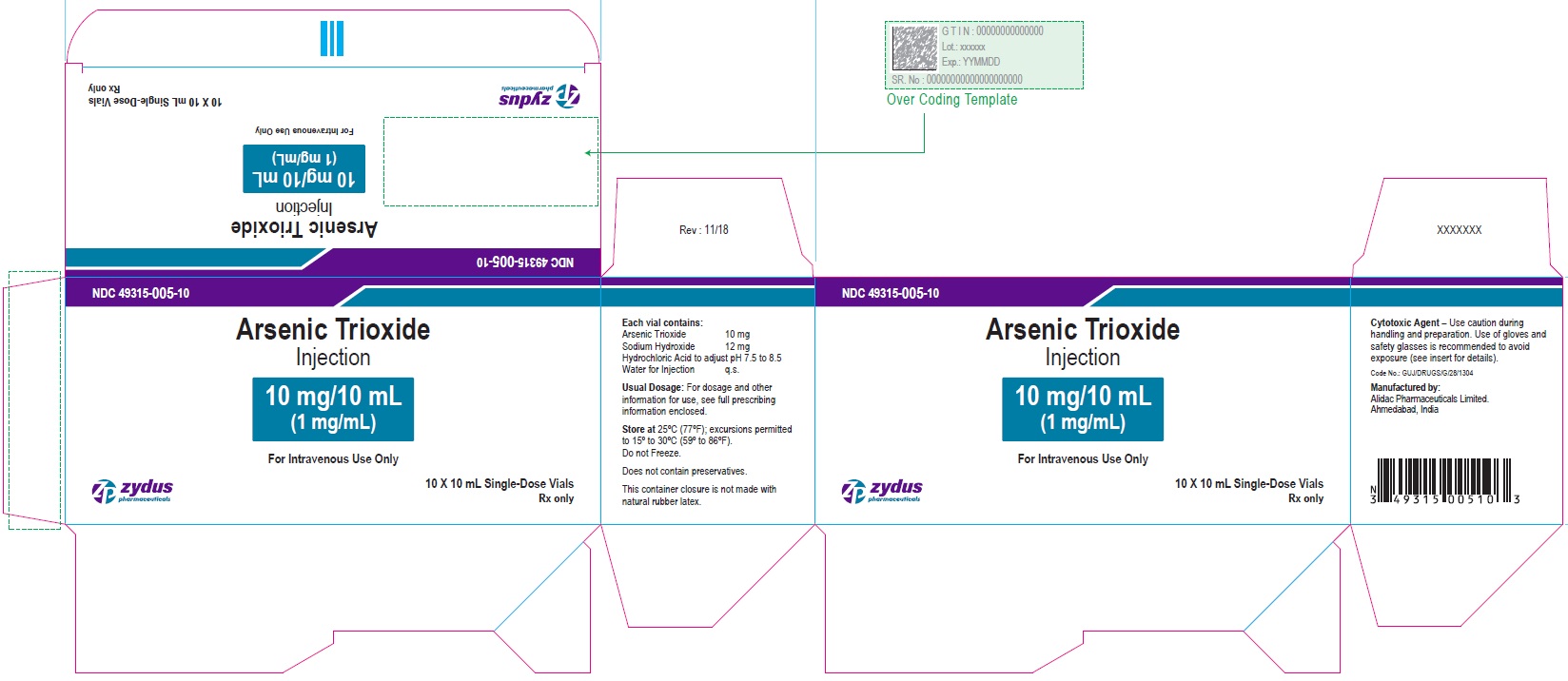 DRUG LABEL: Arsenic trioxide
NDC: 49315-005 | Form: INJECTION, SOLUTION
Manufacturer: Zydus Lifesciences Limited
Category: prescription | Type: HUMAN PRESCRIPTION DRUG LABEL
Date: 20221105

ACTIVE INGREDIENTS: ARSENIC TRIOXIDE 1 mg/1 mL
INACTIVE INGREDIENTS: SODIUM HYDROXIDE; HYDROCHLORIC ACID; WATER

ARSENIC TRIOXIDE INJECTION

PRINCIPAL DISPLAY PANEL - Vial Label

NDC 49315-005-01

Arsenic Trioxide Injection

10 mg/10 mL

(1 mg/mL)

For Intravenous Use Only

Cytotoxic Agent

10 mL Single-Dose Vial

Rx only

Zydus Pharmaceuticals

PRINCIPAL DISPLAY PANEL - Carton Label

NDC 49315-005-10

Arsenic Trioxide Injection

10 mg/10 mL

(1 mg/mL)

For Intravenous Use Only

10 X 10 mL Single-Dose Vials

Rx only

Zydus Pharmaceuticals